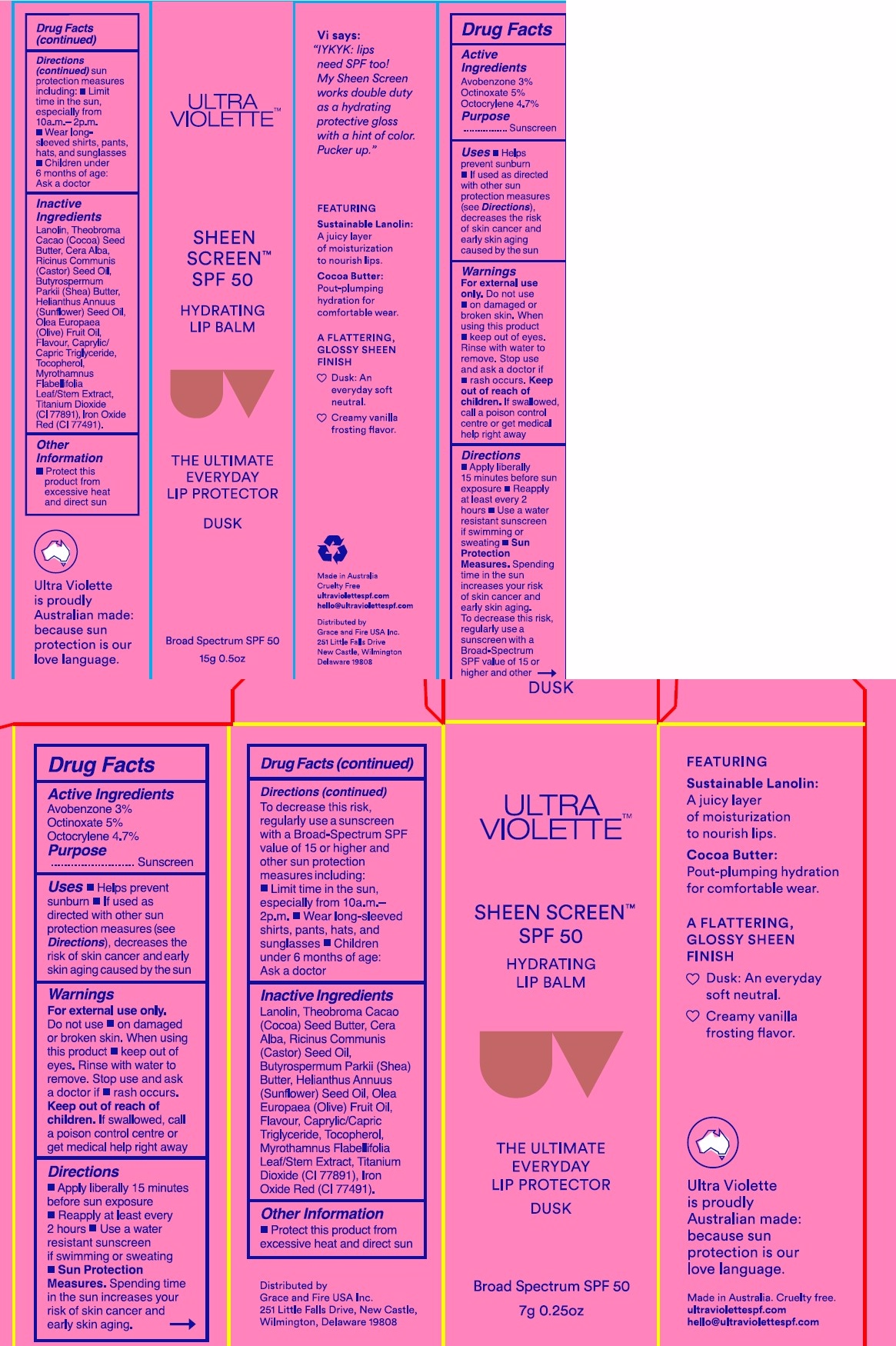 DRUG LABEL: Ultra Violette Sheen Screen Broad Spectrum Hydrating Lip Balm Dusk
NDC: 84803-104 | Form: OINTMENT
Manufacturer: Grace And Fire USA Inc.
Category: otc | Type: HUMAN OTC DRUG LABEL
Date: 20260106

ACTIVE INGREDIENTS: OCTINOXATE 5 g/100 g; AVOBENZONE 3 g/100 g; OCTOCRYLENE 4.7 g/100 g
INACTIVE INGREDIENTS: LANOLIN; TITANIUM DIOXIDE; BUTYROSPERMUM PARKII (SHEA) BUTTER; WHITE WAX; CAPRYLIC/CAPRIC TRIGLYCERIDE; CI 77491; MYROTHAMNUS FLABELLIFOLIA TOP; THEOBROMA CACAO (COCOA) SEED BUTTER; HELIANTHUS ANNUUS (SUNFLOWER) SEED OIL; OLEA EUROPAEA (OLIVE) FRUIT OIL; TOCOPHEROL; RICINUS COMMUNIS (CASTOR) SEED OIL

Ultra Violette Sheen Screen Broad Spectrum Hydrating Lip Balm Dusk

Active Ingredients

Avobenzone 3%

Octinoxate 5%

Octocrylene 4.7%

Purpose

Sunscreen

Uses

- Helps Prevent Sunburn

- if used as directed with other sun protection measures (see Directions) ,decreases the risk of skin cancer and early skin aging caused by the sun

Warnings

For External use Only

Do not use

- on damaged or broken skin, when using this product

- keep out of eyes rinse with water to remove

Stop use and ask doctor if

- rash occur

Keep out of reach of children

if swallowed , call a poison control centre or get medical help right away

Directions

* Apply liberally 15 minutes before sun exposure
* Reapply at least every 2 hours • Use a water resistant sunscreen if swimming or sweating
* Sun Protection
Measures. Spending time in the sun increases your risk of skin cancer and early skin aging

To decrease this risk, regularly use a sunscreen with a Broad-Spectrum SPF value of 15 or higher and other sun protection measures including:
* Limit time in the sun, especially from 10a.m.- 2p.m. • Wear long-sleeved shirts, pants, hats, and sunglasses • Children under 6 months of age: Ask a doctor

Inactive Ingredients

Lanolin, Theobroma Cacao (Cocoa) Seed Butter, Cera Alba, Ricinus Communis (Castor) Seed Oil, Butyrospermum Parkii (Shea)
Butter, Helianthus Annuus (Sunflower) Seed Oil, Olea Europaea (Olive) Fruit Oil, Flavour, Caprylic/Capric Triglyceride, Tocopherol, Myrothamnus Flabellifolia Leaf/Stem Extract, Titanium Dioxide (Cl 77891), Iron Oxide Red (CI 77491).

Other Information

Protect this product from excessive heat and direct sun